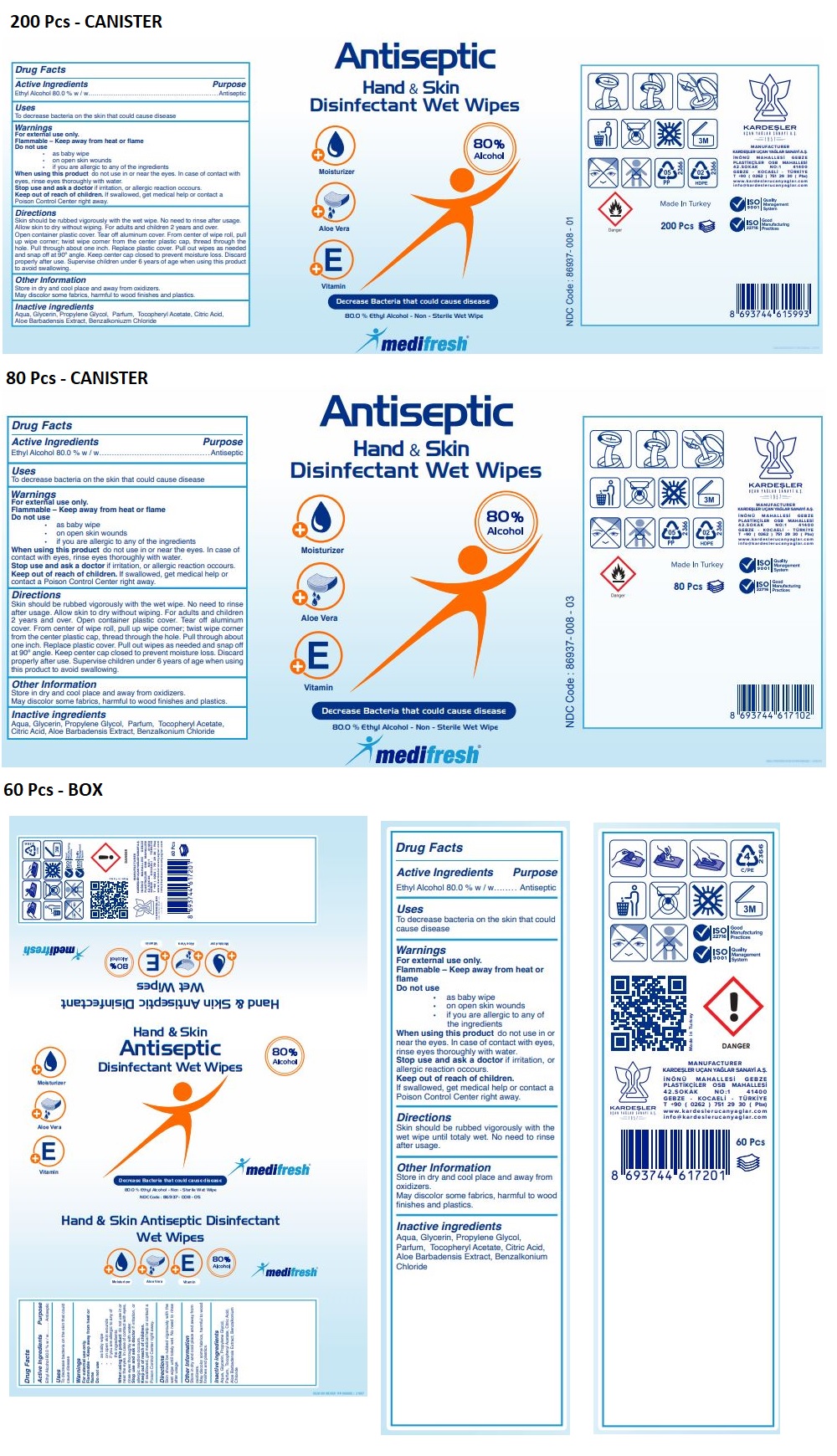 DRUG LABEL: medifresh Antiseptic Hand and Skin Disinfectant Wet Wipes
NDC: 86937-008 | Form: CLOTH
Manufacturer: KARDESLER UCAN YAGLAR SANAYI ANONIM SIRKETI
Category: otc | Type: HUMAN OTC DRUG LABEL
Date: 20220623

ACTIVE INGREDIENTS: ALCOHOL 80 g/100 g
INACTIVE INGREDIENTS: WATER; GLYCERIN; PROPYLENE GLYCOL; .ALPHA.-TOCOPHEROL ACETATE; CITRIC ACID MONOHYDRATE; ALOE VERA LEAF; BENZALKONIUM CHLORIDE

medifresh® Antiseptic Hand & Skin Disinfectant Wet Wipes

Active Ingredients

Ethyl Alcohol 80.0 % w / w

Purpose

Antiseptic

Uses

To decrease bacteria on the skin that could cause disease

Warnings

For external use only.

Flammable – Keep away from heat or flame

Do not use
• as baby wipe
• on open skin wounds
• if you are allergic to any of the ingredients

When using this product do not use in or near the eyes. In case of contact with eyes, rinse eyes thoroughly with water.

Stop use and ask a doctor if irritation, or allergic reaction occurs.

Keep out of reach of children. If swallowed, get medical help or contact a Poison Control Center right away.

Directions

Skin should be rubbed vigorously with the wet wipe. No need to rinse after usage. Allow skin to dry without wiping. For adults and children 2 years and over. Open container plastic cover. Tear off aluminum cover. From center of wipe roll, pull up wipe corner; twist wipe corner from the center plastic cap, thread through the hole. Pull through about one inch. Replace plastic cover. Pull out wipes as needed and snap off at 90º angle. Keep center cap closed to prevent moisture loss. Discard properly after use. Supervise children under 6 years of age when using this product to avoid swallowing.

Other Information

Store in dry and cool place and away from oxidizers.

May discolor some fabrics, harmful to wood finishes and plastics.

Inactive ingredients

Aqua, Glycerin, Propylene Glycol, Parfum, Tocopheryl Acetate, Citric Acid, Aloe Barbadensis Extract, Benzalkonium Chloride

Moisturizer

Aloe Vera

Vitamin E

Decrease Bacteria that could cause disease

Non - Sterile Wet Wipe

MANUFACTURER
KARDEŞLER UÇAN YAĞLAR SANAYİ A.Ş.
İNÖNÜ MAHALLESİ GEBZE
PLASTİKÇİLER OSB MAHALLESİ
42.SOKAK NO:1 41400
GEBZE - KOCAELİ - TÜRKİYE
T +90 (0262) 751 29 30 (Pbx)
www.kardeslerucanyaglar.com
info@kardeslerucanyaglar.com

Made In Turkey